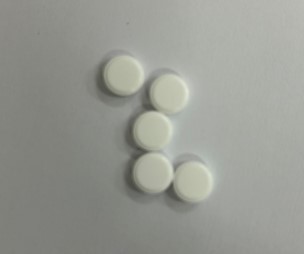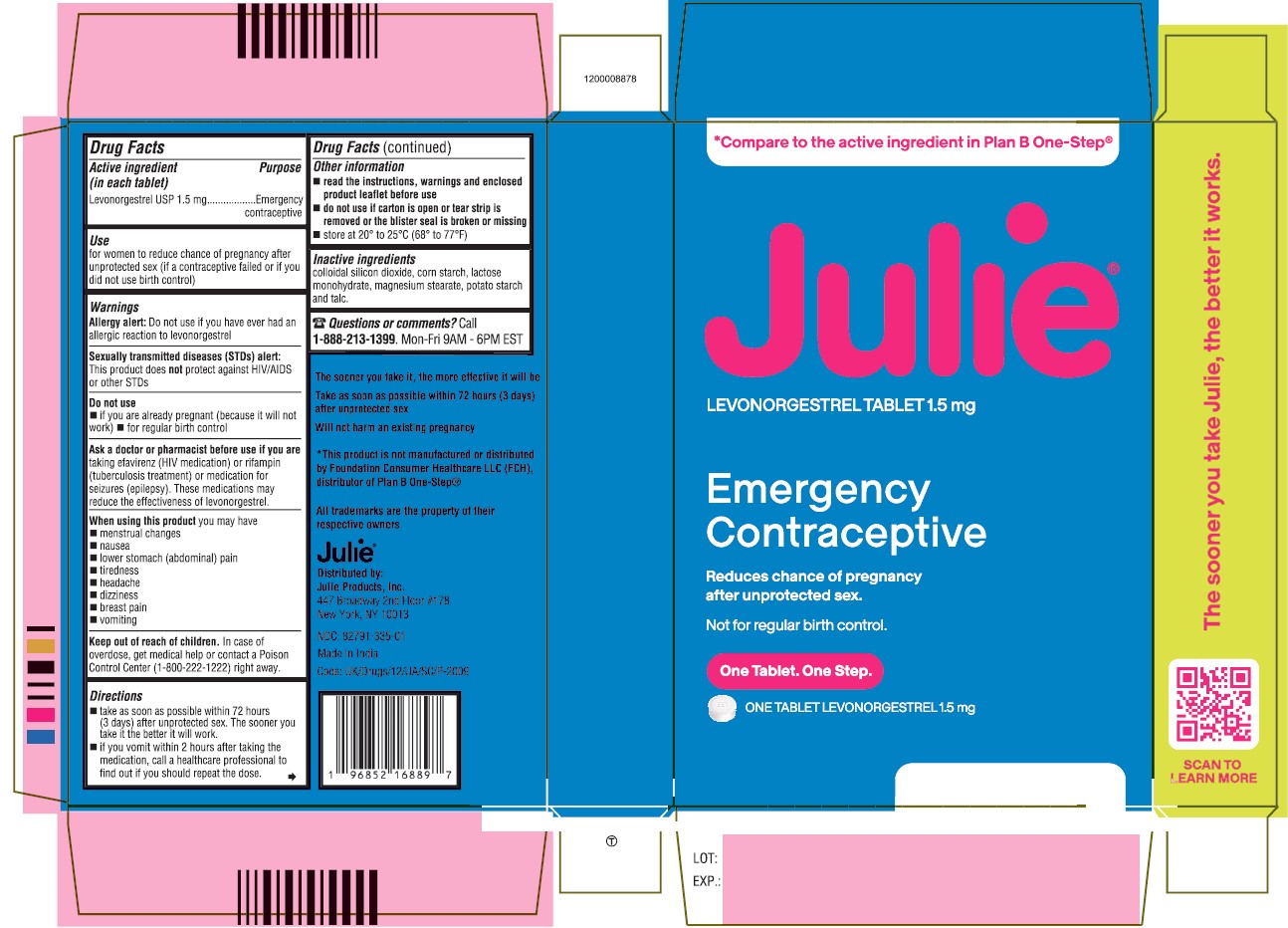 DRUG LABEL: Julie
NDC: 82791-335 | Form: TABLET
Manufacturer: Julie Products Inc
Category: otc | Type: HUMAN OTC DRUG LABEL
Date: 20250714

ACTIVE INGREDIENTS: LEVONORGESTREL 1.5 mg/1 1
INACTIVE INGREDIENTS: STARCH, CORN; WATER; SILICON DIOXIDE; TALC; STARCH, POTATO; LACTOSE MONOHYDRATE; MAGNESIUM STEARATE

Active Ingredient (in each tablet)

Levonorgestrel 1.5 mg

Purpose

Emergency contraceptive

Use

For women to reduce chance of pregnancy after unprotected sex (if a contraceptive failed or if you did not use birth control)

Directions

- Take as soon as possible within 72 hours (3 days) after unprotected sex. The sooner you take it the better it will work.
- If you vomit within 2 hours after taking the medication, call a healthcare professional to find out if you should repeat the dose.

Warnings

Allergy Alert: Do not use if you have ever had an allergic reaction to levonorgestrel
Sexually transmitted diseases (STDs) Alert: This product does not protect against HIV/AIDS or other STDs

Do Not Use

- If you are already pregnant (because it will not work)
- For regular birth control

Ask a Doctor or Pharmacist Before Use If You Are

taking efavirenz (HIV medication) or rifampin (tuberculosis treatment) or medication for seizures (epilepsy). These medications may reduce the effectiveness of levonorgestrel.

When Using

When using this product you may experience:

- Menstrual changes
- Nausea
- Lower stomach (abdominal) pain
- Tiredness
- Headaches
- Dizziness
- Breast pain
- Vomiting

Keep Out of Reach of Children

In case of overdose, get medical help or contact a Poison Control Center (1-800-222-1222) right away.

Other Information

- Read the instructions, warnings and enclosed product leaflet before use
- Do not use if carton is open or tear strip is removed or the blister seal is broken or missing
- Store at 20° to 25°C (68° to 77°F)

Inactive Ingredients

Colloidal Silicon Dioxide, Corn Starch, Lactose Monohydrate, Magnesium Stearate, Potato Starch, Talc, & Purified Water

Questions?

Call 1-888-213-1399. Monday- Friday 9 AM- 6 PM EST.

Julie Products, Inc.,
New York 10013

Product made in India

Information for Patients

JulieTM

LEVONORGESTREL TABLET 1.5 MG

- Emergency Contraceptive
- One Tablet. One Step.
- What You Need To Know

What is Julie™?

Julie™ is emergency contraception that helps prevent pregnancy after birth control failure or unprotected sex. It is a backup method of preventing pregnancy and should not be used as regular birth control.

What Julie™ is not.

Julie™ will not work if you are already pregnant and will not affect an existing pregnancy. Julie™ will not protect you from HIV infection (the virus that causes AIDS) and other sexually transmitted diseases (STDs).

When should I use Julie™?

The sooner you take emergency contraception, the better it works. You should use Julie™ within 72 hours (3 days) after you have had unprotected sex.

Julie™ is a backup or emergency method of birth control you can use when:

- Your regular birth control was used incorrectly or failed
- You did not use any birth control method

When not to use Julie™.

Julie™ should not be used:

- As a regular birth control method, because it's not as effective as regular birth control.
- If you are already pregnant, because it will not work.
- If you are allergic to levonorgestrel or any other ingredients in Julie™.

When should I talk to a doctor or pharmacist?

Ask a doctor or pharmacist before use if you are taking efavirenz (HIV medication) or rifampin (tuberculosis treatment) or medication for seizures (epilepsy). These medications may reduce the effectiveness of Julie™ and increase your chance of becoming pregnant. Your doctor may prescribe another form of emergency contraception that may not be affected by these medications.

How does Julie™ work?

Julie works before release of an egg from the ovary. As a result, Julie usually stops or delays TM the release of an egg from the ovary. Julie is one tablet that contains a higher dose of levonorgestrel than birth control pills and works in a similar way to prevent pregnancy.

How can I get the best results from Julie™?

You have 72 hours (3 days) to try to prevent pregnancy after birth control failure or unprotected sex. The sooner you take Julie™, the better it works.

How effective is Julie™?

If Julie™ is taken as directed, it can significantly decrease the chance that you will get pregnant. About 7 out of every 8 women who would have gotten pregnant will not become pregnant.

How will I know Julie™ worked?

You will know Julie™ has been effective when you get your next period, which should come at the expected time, or within a week of the expected time. If your period is delayed beyond 1 week, it is possible you may be pregnant. You should get a pregnancy test and follow up with your healthcare professional.

Will I experience any side effects?

- Some women may have changes in their period, such as a period that is heavier or lighter or a period that is early or late. If your period is more than a week late, you may be pregnant.
- If you have severe abdominal pain, you may have an ectopic pregnancy, and should get immediate medical attention.
- When used as directed, Julie™ is safe and effective. Side effects may include changes in your period, nausea, lower stomach (abdominal) pain, tiredness, headache, dizziness, and breast tenderness.
- If you vomit within 2 hours of taking the medication, call a healthcare professional to find out if you should repeat the dose.

What if I still have questions about Julie™?

If you have questions or need more information, call our toll free number, 1-888-213-1399. Monday- Friday 9 AM- 6 PM EST.

PACKAGE LABEL-PRINCIPAL DISPLAY PANEL -1.5 mg (1 Tablet Carton Label)

One tablet. One step.
JulieTM
LEVONORGESTREL TABLET 1.5 mg
Emergency Contraceptive
Reduces chance of pregnancy after unprotected sex.
Not for regular birth control.

One Tablet

Levonorgestrel 1.5 mg